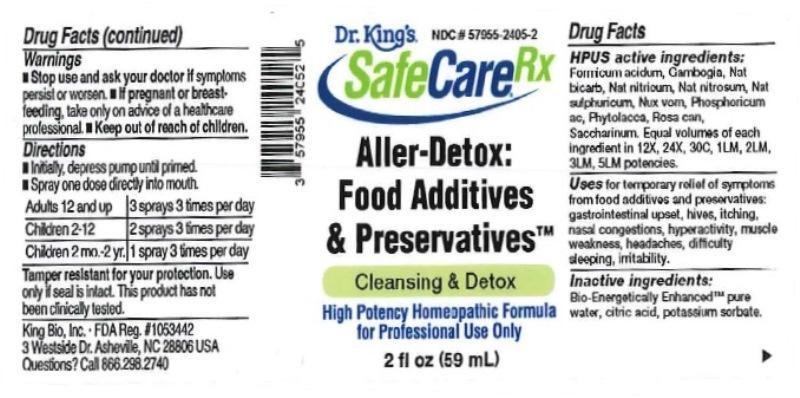 DRUG LABEL: Aller-Detox Food Additives and Preservatives
NDC: 57955-2405 | Form: LIQUID
Manufacturer: King Bio Inc.
Category: homeopathic | Type: HUMAN OTC DRUG LABEL
Date: 20161220

ACTIVE INGREDIENTS: FORMIC ACID 12 [hp_X]/59 mL; GAMBOGE 12 [hp_X]/59 mL; SODIUM BICARBONATE 12 [hp_X]/59 mL; SODIUM NITRATE 12 [hp_X]/59 mL; SODIUM NITRITE 12 [hp_X]/59 mL; SODIUM SULFATE 12 [hp_X]/59 mL; STRYCHNOS NUX-VOMICA SEED 12 [hp_X]/59 mL; PHOSPHORIC ACID 12 [hp_X]/59 mL; PHYTOLACCA AMERICANA ROOT 12 [hp_X]/59 mL; ROSA CANINA FRUIT 12 [hp_X]/59 mL; SACCHARIN 12 [hp_X]/59 mL
INACTIVE INGREDIENTS: WATER; ANHYDROUS CITRIC ACID; POTASSIUM SORBATE

Aller-Detox: Food Additives and Preservatives

Drug Facts

____________________________________________________________________________________________________________________

HPUS active ingredients: Formicum acidum, Gambogia, Natrum bicarbonicum, Natrum nitricum, Natrum nitrosum, Natrum sulphuricum, Nux vomica, Phosphoricum acidum, Phytolacca decandra, Rosa canina, Saccharinum. Equal volumes of each ingredient in 12X, 24X, 30C, 1LM, 2LM, 3LM, 5LM potencies.

INDICATIONS AND USAGE

Uses for relief of symptoms from food additives and preservatives:

- gastrointestinal upset
- hives
- itching
- nasal congestions
- hyperactivity
- muscle weakness
- headaches
- difficulty sleeping
- irritability

INACTIVE INGREDIENT

Inactive ingredients: Bio-Energetically Enhanced pure water base, citric acid, potassium sorbate.

Warnings

- Stop use and ask your doctor if symptoms persist or worsen.
- If pregnant or breast-feeding, take only on advice of a healthcare professional.

- Keep out of reach of children.

Directions:

- Initially, depress pump until primed.
- Spray one dose directly into mouth.
- Adults: 3 sprays 3 times per day.
- Children 2-12 years: 2 sprays 3 times per day.
- Children 2 mo - 2 yr.: 1 spray 3 times per day.

OTHER SAFETY INFORMATION

Tamper resistant for your protection. Use only if safety seal is intact. This product has not been clinically tested.

PURPOSE

Uses a natural aid for: gastrointestinal upset, hives, itching, nasal congestions, hyperactivity, muscle weakness, headaches, difficulty sleeping, irritability.